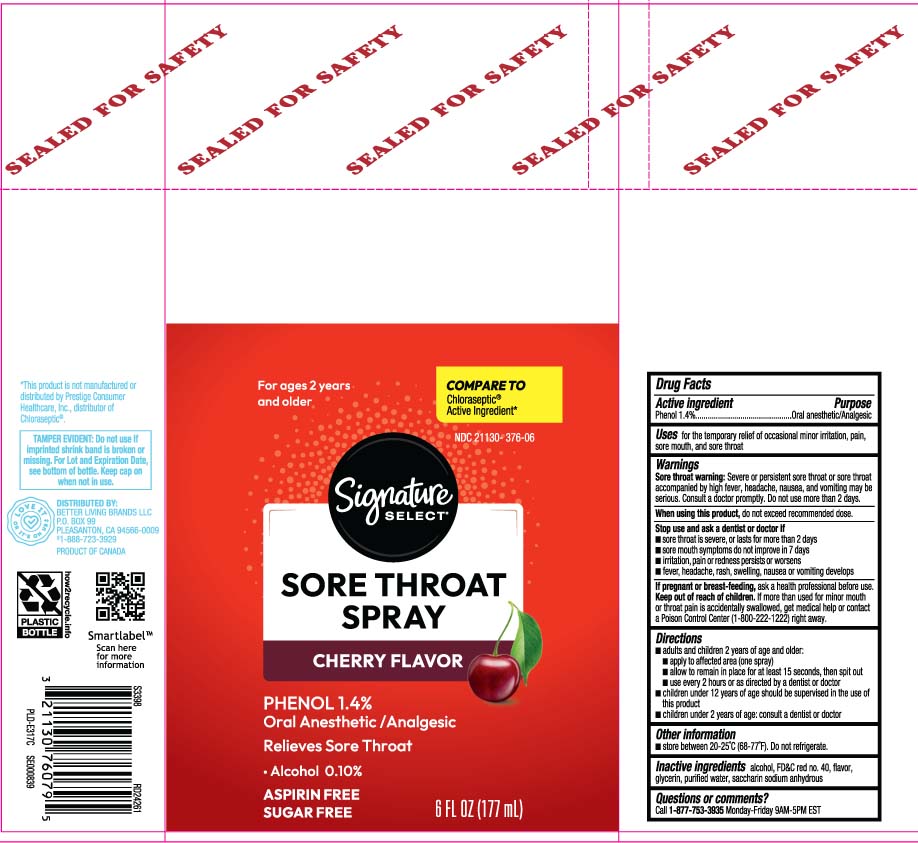 DRUG LABEL: Sore Throat
NDC: 21130-376 | Form: SPRAY
Manufacturer: Safeway, Inc.
Category: otc | Type: HUMAN OTC DRUG LABEL
Date: 20241114

ACTIVE INGREDIENTS: PHENOL 1.4 g/100 mL
INACTIVE INGREDIENTS: ALCOHOL; FD&C RED NO. 40; GLYCERIN; WATER; SACCHARIN SODIUM

Drug Facts

Active ingredient

Phenol 1.4%

Purpose

Oral Anesthetic/Analgesic

Uses

for the temporary relief of occasional minor irritation, pain, sore mouth, and sore throat

Warnings

Sore throat warning: Severe or persistent sore throat or sore throat accompanied by high fever, headache, nausea, and vomiting may be serious. Consult a doctor promptly. Do not use more than 2 days or administer to children under 3 years of age unless directed by a doctor.

When using this product,

do not exceed recommended dose.

Stop use and ask a dentist or doctor if

- sore throat is severe, or lasts for more than 2 days
- sore mouth symptoms do not improve in 7 days
- irritation, pain or redness persists or worsens
- fever, headache, rash, swelling, nausea or vomiting develops

If pregnant or breast-feeding,

ask a health professional before use.

Keep out of reach of children.

If more than used for minor mouth or throat pain accidentally swallowed, get medical help or contact a Poison Control Center (1-800-222-1222) right away.

Directions

- adults and children 2 years of age and older
  - apply to affected area (one spray)
  - allow to remain in place for at least 15 seconds, then spit out
  - use every 2 hours as directed by a doctor or dentist
- children under 12 years of age should be supervised in the used in this product
- children under 2 years of age, consult a doctor or dentist

Other information

- store between 20º-25ºC (68º-77ºF). Do not refrigerate.

Inactive ingredients

alcohol, FD&C red #40, flavor, glycerin, purified water, saccharin sodium anhydrous

Questions or comments?

Call 1-877-753-3935 Monday-Friday 9AM-5PM EST

Principal Display Panel

COMPARE TO Chloraseptic® Active Ingredient*

SORE THROAT SPRAY

CHERRY FLAVOR

PHENOL 1.4 %

Oral Anesthetic / Analgesic

Relieves Sore Throat

Alcohol 0.10%

ASPIRIN FREE

SUGAR FREE

FL OZ (mL)

*This product is not manufactured or distributed by Prestige Brands Inc., distributor of Chloraseptic®.

TAMPER EVIDENT: Do not use if imprinted shrink band is broken or missing. For Lot and Expiration Date, see bottom of bottle. Keep capon when not in use.

DISTRIBUTED BY

BETTER LIVING BRAND LLC

P.O. BOX 99, PLEASANTON, CA 94566-0009

Package Label

SIGNATURE SELECT Sore Throat Spray Cherry Flavor